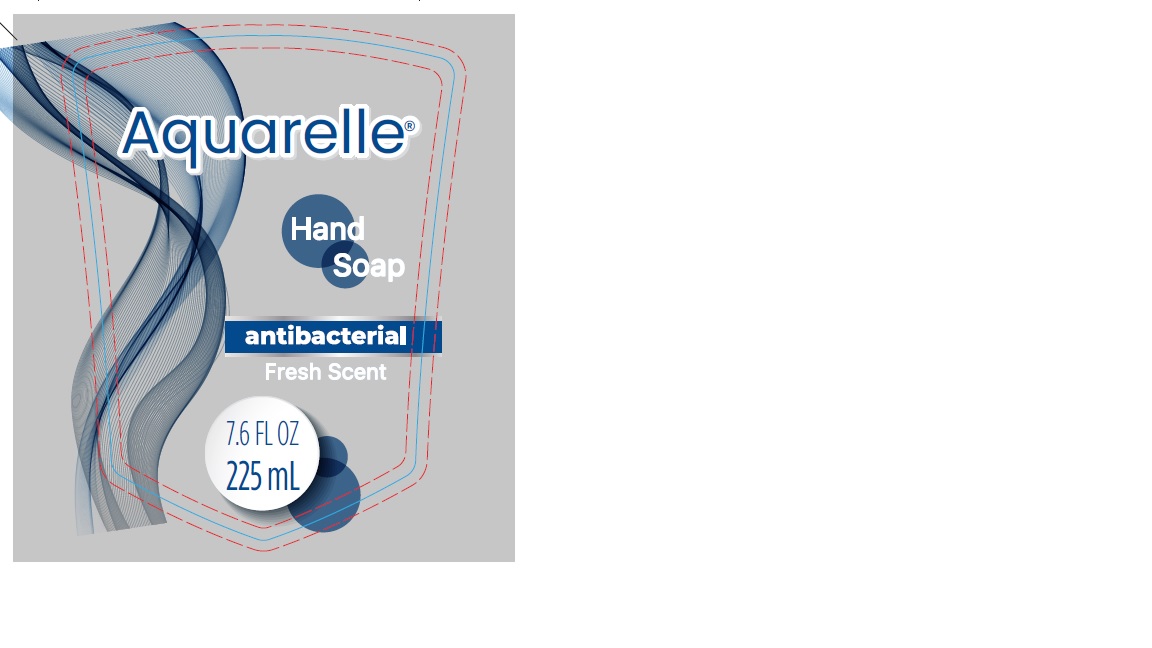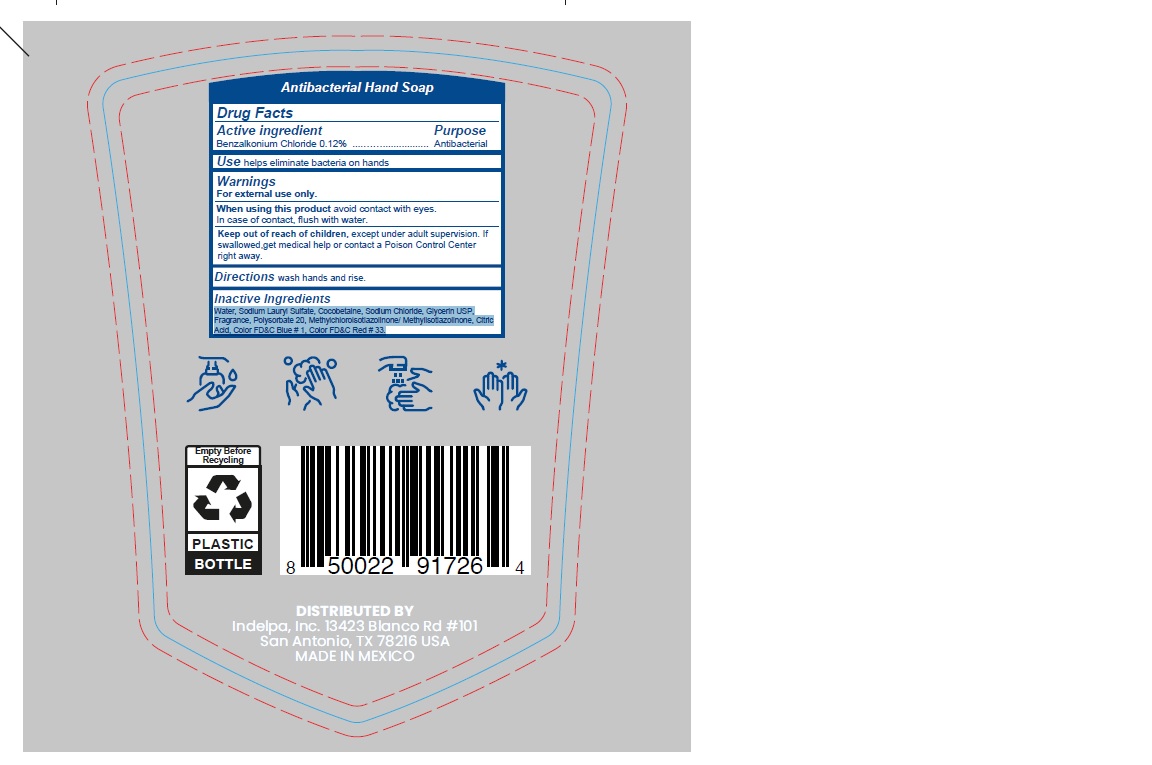 DRUG LABEL: AQUARELLE
NDC: 70697-804 | Form: LIQUID
Manufacturer: INDELPA, S.A DE C.V
Category: otc | Type: HUMAN OTC DRUG LABEL
Date: 20240101

ACTIVE INGREDIENTS: BENZALKONIUM CHLORIDE 0.12 g/100 mL
INACTIVE INGREDIENTS: SODIUM LAURETH SULFATE 8.5 mg/100 mL; GLYCERIN 2.5 mg/100 mL; COCAMIDOPROPYL BETAINE 3 mg/100 mL; CITRIC ACID MONOHYDRATE 0.0087 mg/100 mL; POLYSORBATE 20 0.3 mg/100 mL; METHYLCHLOROISOTHIAZOLINONE/METHYLISOTHIAZOLINONE MIXTURE 0.1 mg/100 mL; SODIUM CHLORIDE 3 mg/100 mL; D&C RED NO. 33 0.000008 mg/100 mL; FD&C BLUE NO. 1 0.000035 mg/100 mL; WATER 82.121 mL/100 mL

ACTIVE INGREDIENT

BENZALKONIUM CHLORIDE 0.12%

Purpose: Antibacterial

INDICATIONS AND USAGE

helps eliminate bacteria on hands

WARNINGS

For external use only.

WHEN USING

avoid contact with eyes.
In case of contact, flush with water.

KEEP OUT OF REACH OF CHILDREN

Except under adult supervision.

If swallowed,get medical help or contact a Poison Control Center right away.

INSTRUCTIONS FOR USE

wash hands and rise.

DOSAGE AND ADMINISTRATION

Liquid.... Topical

INACTIVE INGREDIENT

Water, Sodium Lauryl Sulfate, Cocobetaine, Sodium Chloride, Glycerin USP,
Fragrance, Polysorbate 20, Methylchloroisotiazolinone/ Methylisotiazolinone, Citric
Acid, Color FD&C Blue # 1, Color FD&C Red # 33.

PACKAGE LABEL

Hand Soap Antibacterial Fresh Scent

Hand Soap 250 ml- Dispensing

7.6 fl. oz (250 mL)